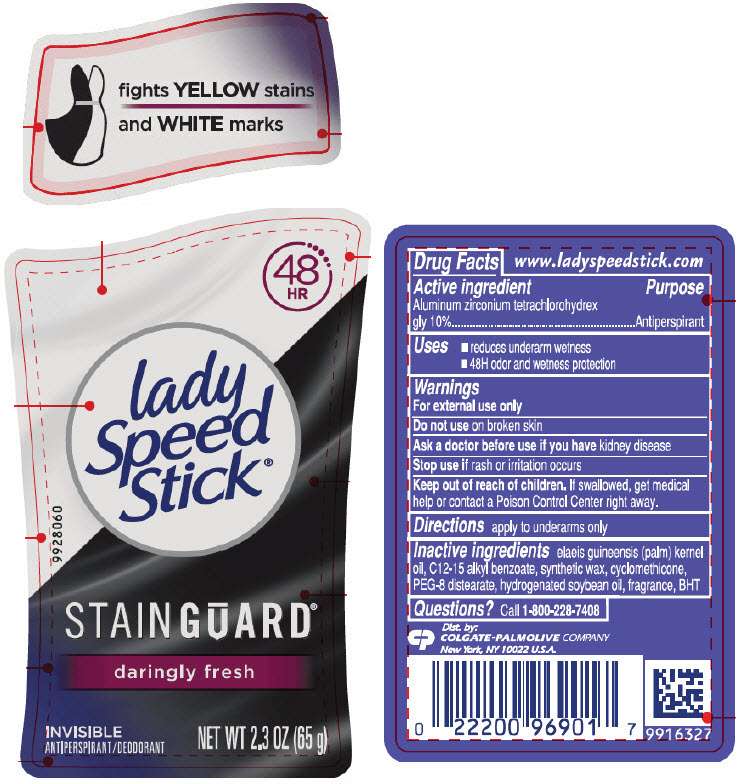 DRUG LABEL: Lady Speed Stick
NDC: 35000-846 | Form: STICK
Manufacturer: COLGATE PALMOLIVE COMPANY
Category: otc | Type: HUMAN OTC DRUG LABEL
Date: 20191227

ACTIVE INGREDIENTS: ALUMINUM ZIRCONIUM TETRACHLOROHYDREX GLY 100 mg/1 g
INACTIVE INGREDIENTS: PALM KERNEL OIL; ALKYL (C12-15) BENZOATE; CYCLOMETHICONE; PEG-8 DISTEARATE; HYDROGENATED SOYBEAN OIL; BUTYLATED HYDROXYTOLUENE

lady
Speed
Stick®
Stainguard®

Drug Facts

Active Ingredient

Aluminum zirconium tetrachlorohydrex gly 10%

Purpose

Antiperspirant

Uses

- reduces underarm wetness
- 24 hour protection

Warnings

For external use only

Do not use on broken skin

Ask a doctor before use if you have kidney disease

Stop use if rash or irritation occurs

Keep out of reach of children. If swallowed, get medical help or contact a Poison Control Center right away.

Directions

apply to underarms only

Inactive ingredients

elaeis guineensis (palm) kernel oil, C12-15 alkyl benzoate, synthetic wax, cyclomethicone, PEG-8 distearate, hydrogenated soybean oil, fragrance, BHT

Questions?

Call toll-free 1-800-228-7408

Dist. by:
COLGATE-PALMOLIVE COMPANY
New York, NY 10022

PRINCIPAL DISPLAY PANEL - 65 g Container Label

fights YELLOW stains
and WHITE marks

48
HR

lady
Speed
Stick®

STAINGUARD®

daringly fresh

INVISIBLE
ANTIPERSPIRANT/DEODORANT

NET WT 2.3 OZ (65 g)

9928060